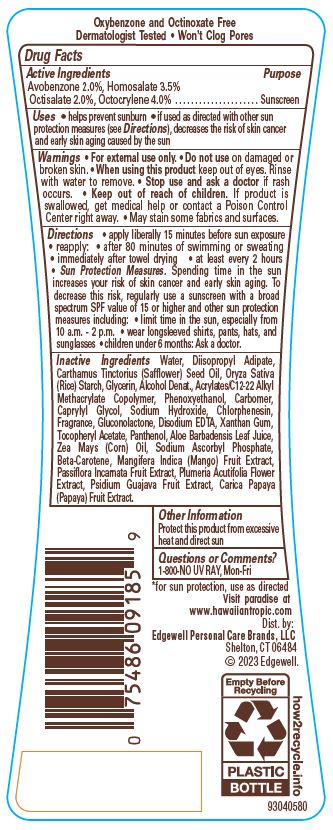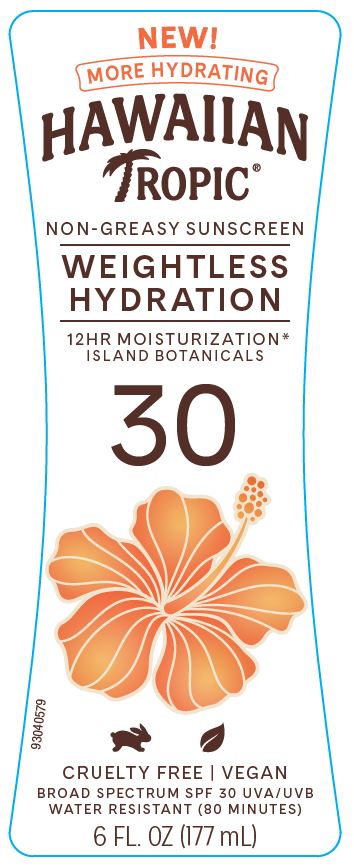 DRUG LABEL: HAWAIIAN TROPIC
NDC: 63354-453 | Form: LOTION
Manufacturer: Edgewell Personal Care Brands LLC
Category: otc | Type: HUMAN OTC DRUG LABEL
Date: 20250928

ACTIVE INGREDIENTS: AVOBENZONE 2 g/100 g; OCTOCRYLENE 4 g/100 g; OCTISALATE 2 g/100 g; HOMOSALATE 3.5 g/100 g
INACTIVE INGREDIENTS: SODIUM HYDROXIDE; EDETATE DISODIUM; ALCOHOL; DIISOPROPYL ADIPATE; XANTHAN GUM; PAPAYA; CARBOMER HOMOPOLYMER, UNSPECIFIED TYPE; GLUCONOLACTONE; SODIUM ASCORBYL PHOSPHATE; WATER; PLUMERIA RUBRA FLOWER; GLYCERIN; MANGO; PHENOXYETHANOL; ALPHA-TOCOPHEROL ACETATE; CORN OIL; PASSIFLORA INCARNATA FRUIT; SAFFLOWER OIL; CHLORPHENESIN; PANTHENOL; ALOE VERA LEAF; STARCH, RICE; GUAVA; CAPRYLYL GLYCOL; BETA CAROTENE

Active Ingredients

Avobenzone 2.0%, Homosalate 3.5%, Octisalate 2.0%, Octocrylene 4.0%

Purpose

Sunscreen

Uses

• helps prevent sunburn • if used as directed with other sun protection measures (see Directions), decreases the risk of skin cancer and early skin aging caused by the sun

Warnings

For external use only. • May stain some fabrics and surfaces.

Do not use

on damaged or broken skin.

When using this product

keep out of eyes. Rinse with water to remove.

Stop use and ask a doctor

if rash occurs.

Keep out of reach of children.

If product is swallowed, get medical help or contact a Poison Control Center right away.

Directions

• apply liberally 15 minutes before sun exposure • reapply: • after 80 minutes of swimming or sweating • immediately after towel drying • at least every 2 hours • Sun Protection Measures. Spending time in the sun increases your risk of skin cancer and early skin aging. To decrease this risk, regularly use a sunscreen with a broad spectrum SPF value of 15 or higher and other sun protection measures including: • limit time in the sun, especially from 10 a.m. - 2 p.m. • wear longsleeved shirts, pants, hats, and sunglasses • children under 6 months: Ask a doctor.

Inactive Ingredients

Water, Diisopropyl Adipate, Carthamus Tinctorius (Safflower) Seed Oil, Oryza Sativa (Rice) Starch, Glycerin, Alcohol Denat., Acrylates/C12-22 Alkyl Methacrylate Copolymer, Phenoxyethanol, Carbomer, Caprylyl Glycol, Sodium Hydroxide, Chlorphenesin, Fragrance, Gluconolactone, Disodium EDTA, Xanthan Gum, Tocopheryl Acetate, Panthenol, Aloe Barbadensis Leaf Juice, Zea Mays (Corn) Oil, Sodium Ascorbyl Phosphate, Beta-Carotene, Mangifera Indica (Mango) Fruit Extract, Passiflora Incarnata Fruit Extract, Plumeria Acutifolia Flower Extract, Psidium Guajava Fruit Extract, Carica Papaya (Papaya) Fruit Extract.

Other Information

Protect this product from excessive heat and direct sun

Questions or Comments?

1-800-NO UV RAY, Mon-Fri

Principal Display Panel

NEW!

MORE HYDRATING

HAWAIIAN TROPIC(R)

NON-GREASY SUNSCREEN

WEIGHTLESS

HYDRATION

12HR MOISTURIZATION*

ISLAND BOTANICALS

30

CRUELTY FREE / VEGAN

BROAD SPECTRUM SPF 30 UVA/UVB

WATER RESISTANT (80 MINUTES)

6 FL. OZ. (177 mL)